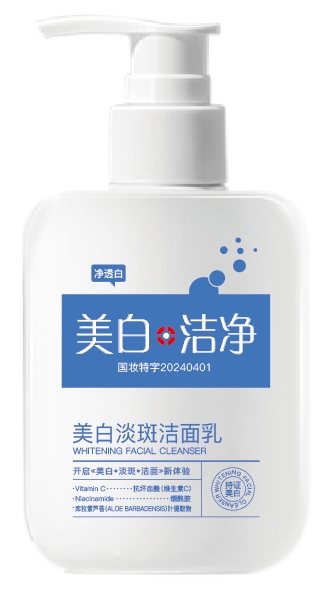 DRUG LABEL: Whitening facial cleanser
NDC: 84507-016 | Form: CREAM
Manufacturer: Guangdong Miaolian Cosmetics Co., Ltd.
Category: otc | Type: HUMAN OTC DRUG LABEL
Date: 20240820

ACTIVE INGREDIENTS: 3-O-ETHYL ASCORBIC ACID 0.4 mg/100 g
INACTIVE INGREDIENTS: WATER

DOSAGE AND ADMINISTRATION

Take appropriate amount of this product on the palm, gently rub with water until it is rich in foam, apply it on the wet face, massage it easily,then rinse by clean water.

WARNINGS

For external use only
Ask a doctor before using. If you have a history of allergies to such products
When using this product avoid contact with the eyes.
if contact occurs, rinse eyes thoroughly with water.Stop use and ask a doctor if condition worsens
condition does not improve after regular use of this product as directed.
Keep outof reach of children.
If pregnant or breast-feeding, please use with care.

INACTIVE INGREDIENT

water..

INDICATIONS AND USAGE

Improve dark yellow, greasy, whitening and whitening.

Keep out of reach of children.

PURPOSE

fades out stubborn dark spots, acne scars,sun spots and blemishes. It helps restore a clearer and more radiant even-toned complexion.